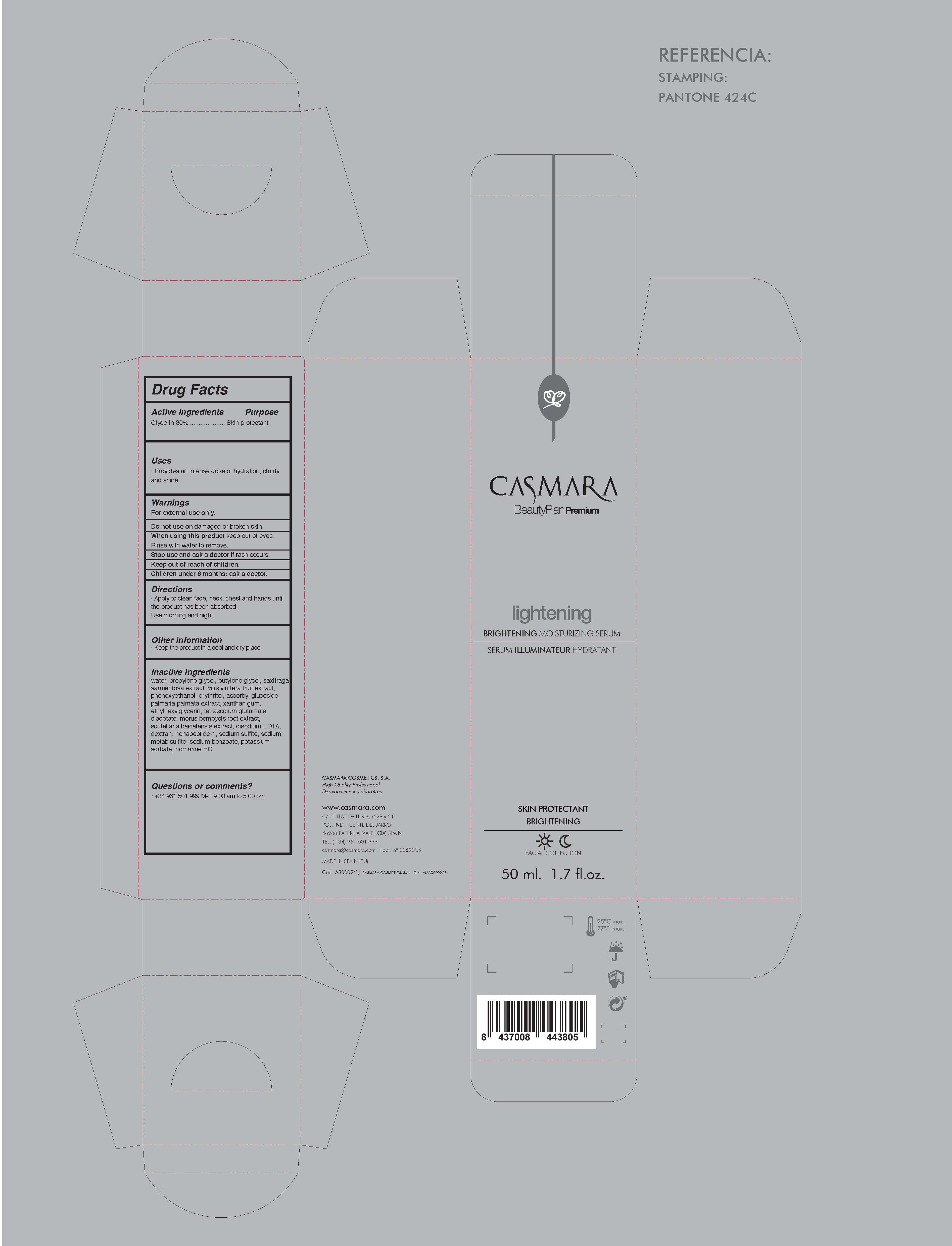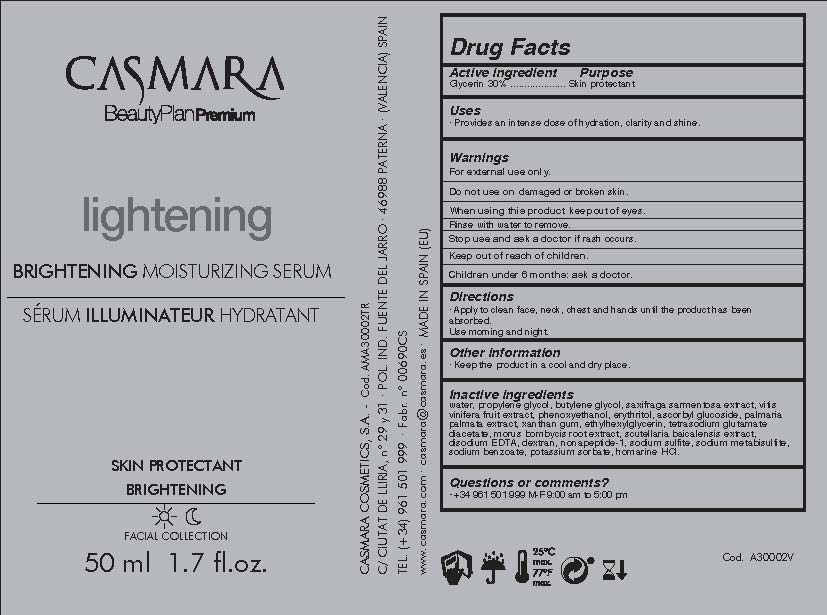 DRUG LABEL: Lightening Brightening Moisturizing Serum
NDC: 20151-102 | Form: CREAM
Manufacturer: Casmara Cosmetics, SA
Category: otc | Type: HUMAN OTC DRUG LABEL
Date: 20170406

ACTIVE INGREDIENTS: GLYCERIN 30 mg/1 mL
INACTIVE INGREDIENTS: XANTHAN GUM 0.1 mg/1 mL; MORUS AUSTRALIS ROOT 0.09 mg/1 mL; BUTYLENE GLYCOL 3.82 mg/1 mL; POTASSIUM SORBATE 0.009 mg/1 mL; WINE GRAPE 1.125 mg/1 mL; ETHYLHEXYLGLYCERIN 0.1 mg/1 mL; WATER 48.935 mg/1 mL; SAXIFRAGA STOLONIFERA LEAF 1.125 mg/1 mL; PHENOXYETHANOL 0.9 mg/1 mL; TETRASODIUM GLUTAMATE DIACETATE 0.094 mg/1 mL; ERYTHRITOL 0.6 mg/1 mL; DULSE 0.225 mg/1 mL; SODIUM METABISULFITE 0.012 mg/1 mL; SODIUM SULFITE 0.012 mg/1 mL; ASCORBYL GLUCOSIDE 0.5 mg/1 mL; NONAPEPTIDE-1 0.06 mg/1 mL; DEXTRAN 40 0.06 mg/1 mL; EDETATE DISODIUM 0.076 mg/1 mL; SCUTELLARIA BAICALENSIS ROOT 0.09 mg/1 mL; PROPANEDIOL 12 mg/1 mL; SODIUM BENZOATE 0.009 mg/1 mL; HOMARINE HYDROCHLORIDE 0.006 mg/1 mL

Lightening Brightening Moisturizing Serum

ACTIVE INGREDIENTS PURPOSE

Glycerin 30%.................... Skin Protectant

Warnings

For external use only.

Do not use on damaged or broken skin.

When using this product keep our of the eyes. Rinse with water to remove.

Stop use and ask a doctor if rash occurs.

Keep out of reach of children.

Whhen using this product do not get into eyes.

Children under 6 months: as a doctor.

WARNINGS

Stop use and ask a doctor if rash occurs

Children under 6 months: ask a doctor

Warnings

Keep out of reach of children

Questions or comments?

+ 34 961 501 999 M-F 9:00 am to 5:00 pm

Other Information

. keep the product in a cool and dry place

Directions

. apply to clean face, neck and chest and hands until the product has been absorbed.

. used in the morning and/or night

DOSAGE AND ADMINISTRATION

. apply to clean face, neck and chest and hands until the product has been absorbed.

. used in the morning and/or night

Uses

. provides an intense dose of hydration, clarity and shine

Inactive Ingredients

Water, Propylene glycol, Butylene glycol, Saxifraga sarmentosa extract, Vitis vinifera fruit extract, Phenoxyethanol, Erythritol, Ascorbyl Glucoside, Palmaria palmata extract, Xanthan gum, Ethylhexylglycerin, Tetrasodium glutamate diacetate, Morus Bombycis Root, Extract, Scutellaria Baicalensis Extract, Disodium EDTA, Dextran, Nonapeptide-1, Sodium sulfite, Sodium metabisulfite, Sodium benzoate, Potassium sorbate, Homarine HCL

Uses

. provides an intense dose of hydration, clarity and shine